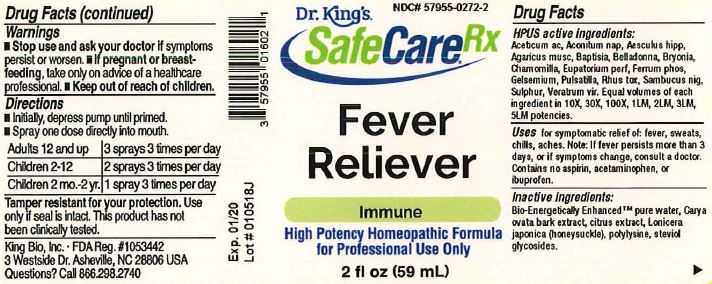 DRUG LABEL: Fever Reliever
NDC: 57955-0272 | Form: LIQUID
Manufacturer: King Bio Inc.
Category: homeopathic | Type: HUMAN OTC DRUG LABEL
Date: 20180206

ACTIVE INGREDIENTS: ACETIC ACID 10 [hp_X]/59 mL; ACONITUM NAPELLUS 10 [hp_X]/59 mL; HORSE CHESTNUT 10 [hp_X]/59 mL; AMANITA MUSCARIA FRUITING BODY 10 [hp_X]/59 mL; BAPTISIA TINCTORIA ROOT 10 [hp_X]/59 mL; ATROPA BELLADONNA 10 [hp_X]/59 mL; BRYONIA ALBA ROOT 10 [hp_X]/59 mL; MATRICARIA CHAMOMILLA 10 [hp_X]/59 mL; EUPATORIUM PERFOLIATUM FLOWERING TOP 10 [hp_X]/59 mL; FERROSOFERRIC PHOSPHATE 10 [hp_X]/59 mL; GELSEMIUM SEMPERVIRENS ROOT 10 [hp_X]/59 mL; PULSATILLA VULGARIS 10 [hp_X]/59 mL; TOXICODENDRON PUBESCENS LEAF 10 [hp_X]/59 mL; SAMBUCUS NIGRA FLOWERING TOP 10 [hp_X]/59 mL; SULFUR 10 [hp_X]/59 mL; VERATRUM VIRIDE ROOT 10 [hp_X]/59 mL
INACTIVE INGREDIENTS: WATER; CARYA OVATA BARK; CITRUS BIOFLAVONOIDS; LONICERA JAPONICA FLOWER; POLYEPSILON-LYSINE (4000 MW); REBAUDIOSIDE A

Fever Reliever™

ACTIVE INGREDIENT

HPUS active ingredients: Aceticum ac, Aconitum nap, Aesculus hipp, Agaricus musc, Baptisia, Belladonna, Bryonia, Chamomilla, Eupatorium perf, Ferrum phos, Gelsemium, Pulsatilla, Rhus tox, Sambucus nig, Sulphur, Veratrum vir.

Equal volumes of each ingredient in 10X, 30X, 100X, 1M, 1LM, 2LM, 3LM, 5LM potencies.

INDICATIONS AND USAGE

Uses for symptomatic relief of: fever, sweats, chills, aches. Note: If fever persists more than 3 days, or if symptoms change, consult a doctor. Contains no aspirin, acetaminophen, or ibuprofen.

Inactive Ingredients:

Bio-Energetically Enhanced™ pure water, Carya ovata bark extract, citrus extract, Lonicera japonica (honeysuckle), polylysine, steviol glycosides.

Warnings

- Stop use and ask your doctor if symptoms persist or worsen.
- If pregnant or breast-feeding, take only on advice of a healthcare professional.

- Keep out of reach of children.

Directions

- Initially, depress pump until primed.
- Spray one dose directly into mouth.
- Adults 12 and up: 3 sprays 3 times per day.
- Children 2-12: 2 sprays 3 times per day.
- Children 2 mo-2 yr: 1 spray 3 times per day.

OTHER SAFETY INFORMATION

Tamper resistant for your protection. Use only if safety seal is intact. This product has not been clinically tested.

PURPOSE

Uses for symptomatic relief of: fever, sweats, chills, aches. Note: If fever persists more than 3 days, or if symptoms change, consult a doctor. Contains no aspirin, acetaminophen, or ibuprofen.